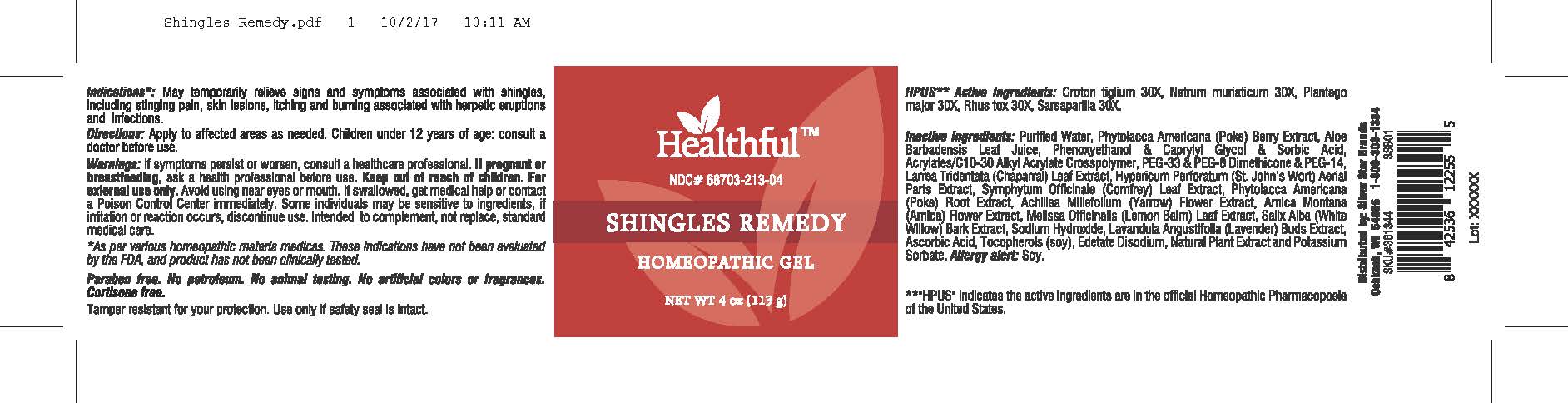 DRUG LABEL: Shingles Remedy
NDC: 68703-213 | Form: GEL
Manufacturer: Silver Star Brands
Category: homeopathic | Type: HUMAN OTC DRUG LABEL
Date: 20250101

ACTIVE INGREDIENTS: PLANTAGO MAJOR 30 [hp_X]/113 g; SODIUM CHLORIDE 30 [hp_X]/113 g; CROTON TIGLIUM SEED 30 [hp_X]/113 g; TOXICODENDRON RADICANS LEAF 30 [hp_X]/113 g; SMILAX ORNATA ROOT 30 [hp_X]/113 g
INACTIVE INGREDIENTS: PHYTOLACCA AMERICANA ROOT; CARBOMER INTERPOLYMER TYPE A (55000 CPS); TOCOPHEROL; POLYETHYLENE GLYCOL 1500; PEG-8 DIMETHICONE; WATER; ACHILLEA MILLEFOLIUM FLOWER; ARNICA MONTANA FLOWER; MELISSA OFFICINALIS LEAF; SALIX ALBA BARK; SODIUM HYDROXIDE; EDETATE DISODIUM; POTASSIUM SORBATE; LAVANDULA ANGUSTIFOLIA FLOWER; ALOE VERA LEAF; ASCORBIC ACID; POLYETHYLENE GLYCOL 700; PHYTOLACCA AMERICANA FRUIT; SORBIC ACID; LARREA TRIDENTATA LEAF; PHENOXYETHANOL; SYMPHYTUM OFFICINALE WHOLE; CAPRYLYL GLYCOL; HYPERICUM PERFORATUM

Healthful™ Shingles Remedy

HPUS** Active Ingredients: Croton tiglium 30X, Natrum muriaticum 30X, Plantago major 30X, Rhus tox 30X, Sarsaprilla 30X.

**"HPUS" indicates the active ingredients are in the official Homeopathic Pharmacopoeia of the United States.

Uses

Indications*: May temporarily relieve signs and symptoms associated with shingles, including stinging pain, skin lesions, itching and burning associated with herpetic eruptions and infections.

*As per various homeopathic materia medicas. These indications have not been evaluated by the FDA, and product has not been clinically tested.

Warnings

If symptoms persist or worsen, consult a healthcare professional. If pregnant or breastfeeding, ask a health professional before use. Keep out of reach of children. For external use only. Avoid using near eyes or mouth. If swallowed, get medical help or contact a Poison Control Center immediately. Some individuals may be sensitive to ingredients, if irritation or reaction occurs, discountinue use. Intended to complement, not replace, standard medical care.

Directions

Apply to affected areas as needed. Children under 12 years of age: consult a doctor before use.

OTHER SAFETY INFORMATION

Paraben free. No petroleum. No animal testing. No artificial colors or fragrances. Cortisone free.

Tamper resistant for your protection. Use only if safety seal is intact.

Inactive Ingredients

Purified Water, Phytolacca Americana (Poke) Berry Extract, Aloe Barbadensis Leaf Juice, Phenoxyethanol & Caprylyl Glycol & Sorbic Acid, Acrylates/C10-30 Alkyl Acrylate Crosspolymer, PEG-33 & PEG-8 Dimethicone & PEG-14, Larrea Tridentata (Chaparral) Leaf Extract, Hypericum Perforatum (St. John's Wort) Aerial Parts Extract, Symphytum Officinale (Comfrey) Leaf Extract, Phytolacca Americana (Poke) Root Extract, Achillea Millefolium (Yarrow) Flower Extract, Arnica Montana (Arnica) Flower Extract, Melissa Officinalis (Lemon Balm) Leaf Extract, Salix Alba (White Willow) Bark Extract, Sodium Hydroxide, Lavandula Angustifolia (Lavender) Buds Extract, Ascorbic Acid, Tocopherols (soy), Edetate Disodium, Natural Plant Extract and Potassium Sorbate. Allergy alert: Soy.

Keep out of reach of children.

PREGNANCY OR BREAST FEEDING

If pregnant or breastfeeding, ask a health professional before use.

PURPOSE

Homeopathic Gel